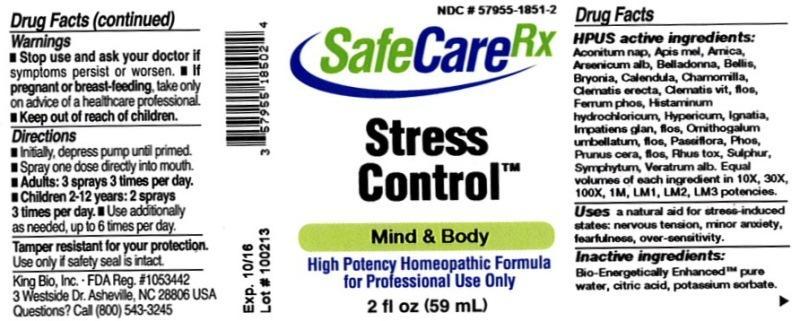 DRUG LABEL: Stress Control
NDC: 57955-1851 | Form: LIQUID
Manufacturer: King Bio Inc.
Category: homeopathic | Type: HUMAN OTC DRUG LABEL
Date: 20131217

ACTIVE INGREDIENTS: ACONITUM NAPELLUS 10 [hp_X]/59 mL; APIS MELLIFERA 10 [hp_X]/59 mL; ARNICA MONTANA 10 [hp_X]/59 mL; ARSENIC TRIOXIDE 10 [hp_X]/59 mL; ATROPA BELLADONNA 10 [hp_X]/59 mL; BELLIS PERENNIS 10 [hp_X]/59 mL; BRYONIA ALBA ROOT 10 [hp_X]/59 mL; CALENDULA OFFICINALIS FLOWERING TOP 10 [hp_X]/59 mL; MATRICARIA RECUTITA 10 [hp_X]/59 mL; CLEMATIS RECTA FLOWERING TOP 10 [hp_X]/59 mL; CLEMATIS VITALBA FLOWER 10 [hp_X]/59 mL; FERROSOFERRIC PHOSPHATE 10 [hp_X]/59 mL; HISTAMINE DIHYDROCHLORIDE 10 [hp_X]/59 mL; HYPERICUM PERFORATUM 10 [hp_X]/59 mL; STRYCHNOS IGNATII SEED 10 [hp_X]/59 mL; IMPATIENS GLANDULIFERA FLOWER 10 [hp_X]/59 mL; ORNITHOGALUM UMBELLATUM 10 [hp_X]/59 mL; PASSIFLORA INCARNATA FLOWERING TOP 10 [hp_X]/59 mL; PHOSPHORUS 10 [hp_X]/59 mL; PRUNUS CERASIFERA FLOWER 10 [hp_X]/59 mL; TOXICODENDRON PUBESCENS LEAF 10 [hp_X]/59 mL; SULFUR 10 [hp_X]/59 mL; COMFREY ROOT 10 [hp_X]/59 mL; VERATRUM ALBUM ROOT 10 [hp_X]/59 mL
INACTIVE INGREDIENTS: WATER; CITRIC ACID MONOHYDRATE; POTASSIUM SORBATE

Stress Control

Drug Facts

____________________________________________________________________________________________________________________

HPUS active ingredients: Aconitum napellus, Apis mellifica, Arnica montana, Arsenicum album, Belladonna, Bellis perennis, Bryonia, Calendula officinalis, Chamomilla, Clematis erecta, Clematis vitalba, flos, Ferrum phosphoricum, Histaminum hydrochloricum, Hypericum perforatum, Ignatia amara, Impatiens glandulifera, flos, Ornithogalum umbellatum, flos, Passiflora incarnata, Phosphorus, Prunus cerasifera, flos, Rhus toxicodendron, Sulphur, Symphytum officinale, Veratrum album. Equal volumes of each ingredient in 10X, 30X, 100X, 1M, LM1, LM2, LM3 potencies.

INDICATIONS AND USAGE

Uses a natural aid for stress-induced states: nervous tension, minor anxiety, fearfulness, over-sinsitivity.

INACTIVE INGREDIENT

Inactive ingredients: Bio-Energetically Enhanced pure water, citric acid, potassium sorbate.

Warnings

- Stop use and ask your doctor if symptoms persist or worsen.
- If pregnant or breast-feeding, take only on advice of a healthcare professional.

- Keep out of reach of children.

Directions:

- Initially, depress pump until primed.
- Spray one dose directly into mouth.
- Adults: 3 sprays 3 times per day.
- Children 2-12 years: 2 sprays 3 times per day.
- Use additionally as needed, up to 6 times per day.

OTHER SAFETY INFORMATION

Tamper resistant for your protection. Use only if safety seal is intact.

PURPOSE

Uses a natural aid for stress-induced states: nervous tension, minor anxiety, fearfulness, over-sensitivity.